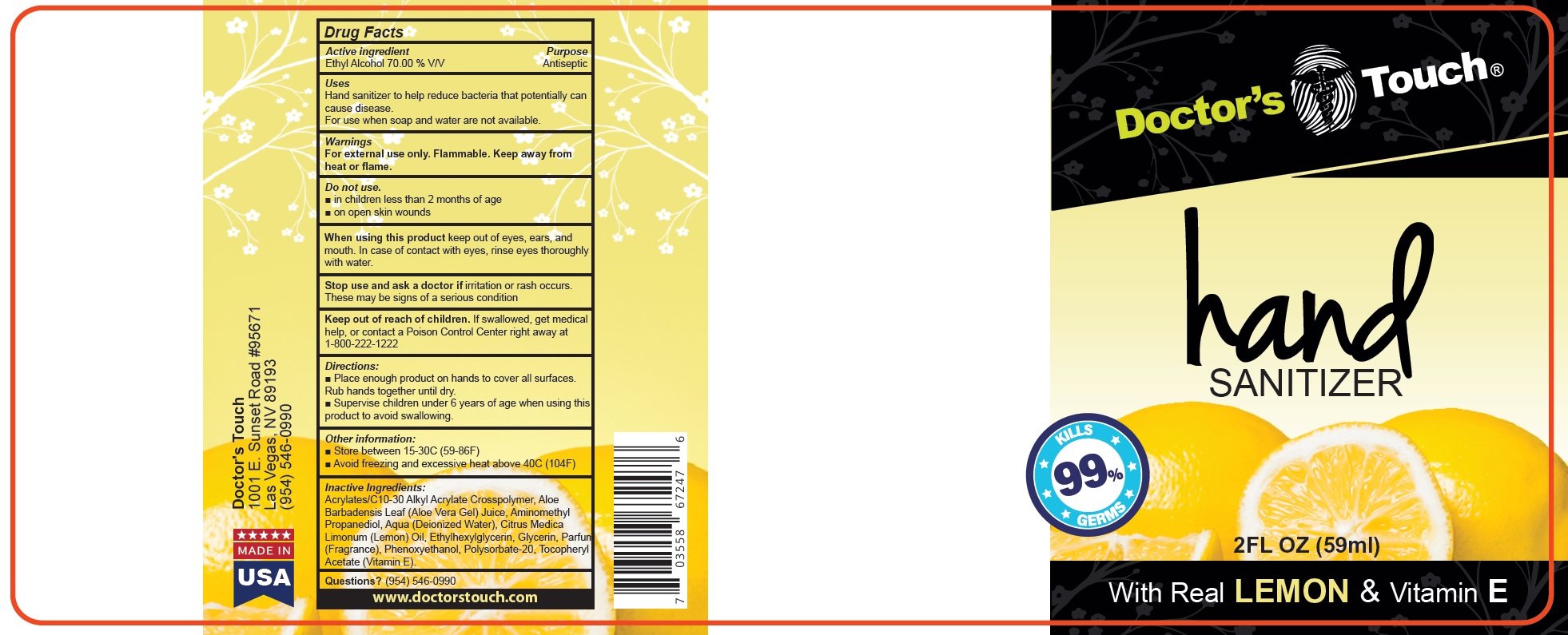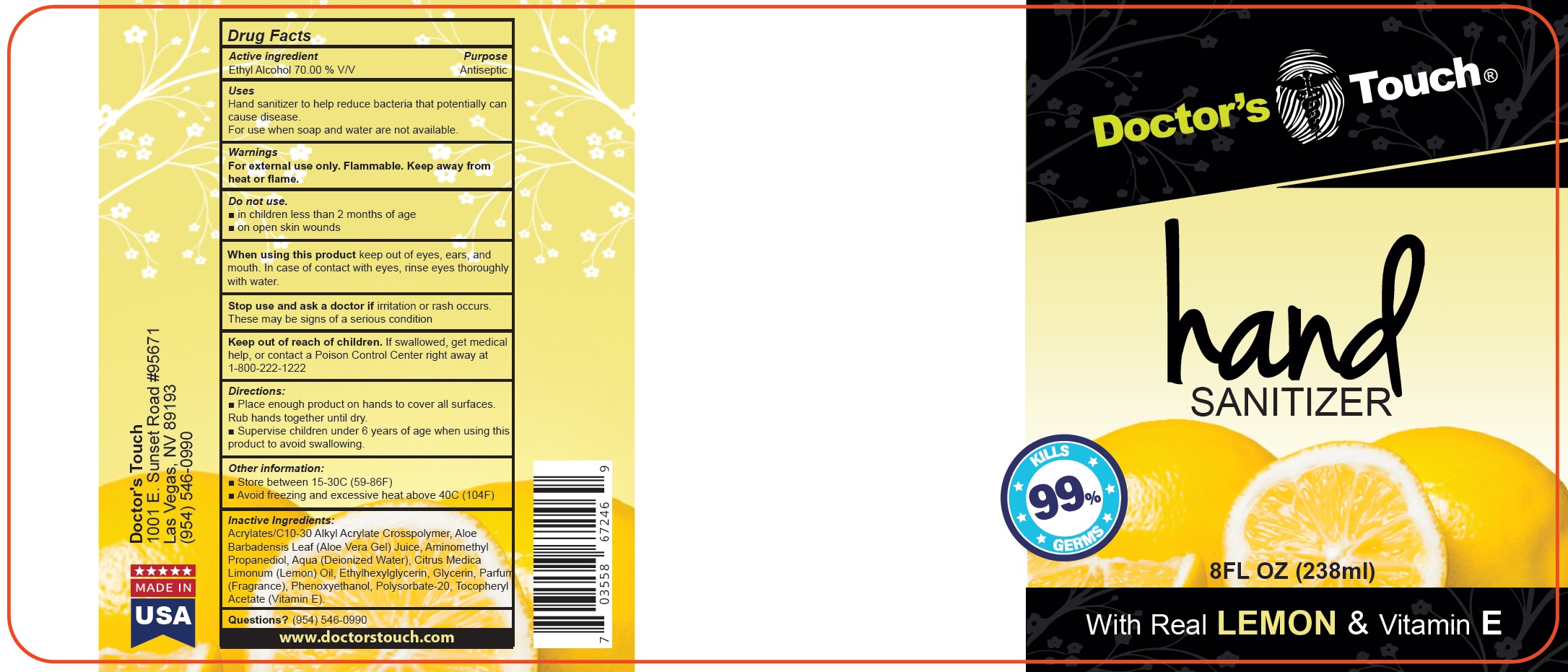 DRUG LABEL: DOCTORS TOUCH Hand Sanitizer
NDC: 80045-313 | Form: LIQUID
Manufacturer: DOCTOR'S CHOICE MEDICAL, LLC
Category: otc | Type: HUMAN OTC DRUG LABEL
Date: 20231111

ACTIVE INGREDIENTS: ALCOHOL 70 mL/100 mL
INACTIVE INGREDIENTS: CARBOMER INTERPOLYMER TYPE A (ALLYL SUCROSE CROSSLINKED); ALOE VERA LEAF; AMINOMETHYL PROPANEDIOL; WATER; LEMON; ETHYLHEXYLGLYCERIN; GLYCERIN; PHENOXYETHANOL; POLYSORBATE 20; .ALPHA.-TOCOPHEROL ACETATE

DOCTOR'S TOUCH Hand Sanitizer

Active ingredient

Ethyl Alcohol 70.00 % V/V

Purpose

Antiseptic

Uses

Hand sanitizer to help reduce bacteria that potentially can cause disease. For use when soap and water are not available.

Warnings

For external use only. Flammable. Keep away from heat or flame.

Do not use.

- in children less than 2 months of age
- on open skin wounds

When using this product

keep out of eyes, ears, and mouth. In case of contact with eyes, rinse eyes thoroughly with water.

Stop use and ask a doctor if

irritation or rash occurs. These may be signs of a serious condition

Keep out of reach of children.

If swallowed, get medical help, or contact a Poison Control Center right away at 1-800-222-1222

Directions:

- Place enough product on hands to cover all surfaces. Rub hands together until dry.
- Supervise children under 6 years of age when using this product to avoid swallowing.

Other information:

- Store between 15-30C (59-86F)
- Avoid freezing and excessive heat above 40C (104F)

Inactive Ingredients:

Acrylates/C10-30 Alkyl Acrylate Crosspolymer, Aloe Barbadensis Leaf (Aloe Vera Gel) Juice, Aminomethyl Propanediol, Aqua (Deionized Water), Citrus Medica Limonum (Lemon) Oil, Ethylhexylglycerin, Glycerin, Parfum(Fragrance), Phenoxyethanol, Polysorbate-20, Tocopheryl Acetate (Vitamin E).

Questions?

(954) 546-0990 www.doctorstouch.com